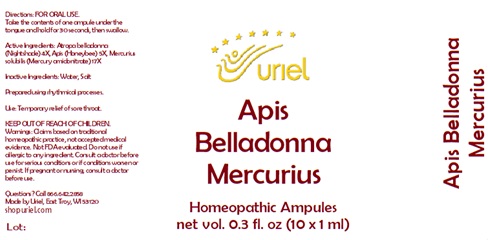 DRUG LABEL: Apis Belladonna Mercurius
NDC: 48951-1214 | Form: LIQUID
Manufacturer: Uriel Pharmacy Inc.
Category: homeopathic | Type: HUMAN OTC DRUG LABEL
Date: 20251106

ACTIVE INGREDIENTS: ATROPA BELLADONNA 4 [hp_X]/1 mL; APIS MELLIFERA 5 [hp_X]/1 mL; MERCURIUS SOLUBILIS 17 [hp_X]/1 mL
INACTIVE INGREDIENTS: WATER; SODIUM CHLORIDE

Apis Belladonna Mercurius

INDICATIONS AND USAGE

Directions: FOR ORAL USE.

DOSAGE AND ADMINISTRATION

Take the contents of one ampule under the tongue and hold for 30 seconds, then swallow.

ACTIVE INGREDIENT

Active Ingredients: Atropa belladonna (Nightshade) 4X, Apis (Honeybee) 5X, Mercurius solubilis (Mercury amidonitrate) 17X

Inactive Ingredients: Water, Salt

Prepared using rhythmical processes.

PURPOSE

Use: Temporary relief of sore throat.

KEEP OUT OF REACH OF CHILDREN.

WARNINGS

Warnings: Claims based on traditional homeopathic practice, not accepted medical evidence. Not FDA evaluated. Do not use if allergic to any ingredient. Consult a doctor before use for serious conditions or if conditions worsen or persist. If pregnant or nursing, consult a doctor before use.

Questions? Call 866.642.2858
Made by Uriel, East Troy, WI 53120
shopuriel.com